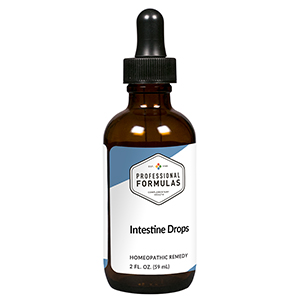 DRUG LABEL: Intestine Drops
NDC: 63083-5009 | Form: LIQUID
Manufacturer: Professional Complementary Health Formulas
Category: homeopathic | Type: HUMAN OTC DRUG LABEL
Date: 20190815

ACTIVE INGREDIENTS: PLANTAGO LANCEOLATA LEAF 3 [hp_X]/59 mL; GENTIANA LUTEA ROOT 5 [hp_X]/59 mL; GOLDENSEAL 5 [hp_X]/59 mL; ULMUS RUBRA BARK 6 [hp_X]/59 mL; BOS TAURUS LARGE INTESTINE 6 [hp_X]/59 mL; SUS SCROFA PARASYMPATHETIC NERVE 30 [hp_X]/59 mL
INACTIVE INGREDIENTS: ALCOHOL; WATER

HID

ACTIVE INGREDIENTS

Plantago lanceolata 3X
Gentiana lutea 5X
Hydrastis canadensis 5X
Ulmus fulva 6X
Large Intestine 6X, 12X, 30X, 60X, 100X
Small Intestine 6X, 12X, 30X, 60X, 100X
Vagus nerve 30X

QUESTIONS

Professional Formulas

PO Box 2034 Lake Oswego, OR 97035

INDICATIONS

For the temporary relief of mild abdominal pain or cramping, bloating, flatulence, constipation, or diarrhea.*

PURPOSE

*Claims based on traditional homeopathic practice, not accepted medical evidence. Not FDA evaluated.

WARNINGS

Consult a doctor if condition worsens or if symptoms persist. Keep out of the reach of children. In case of overdose, get medical help or contact a poison control center right away. If pregnant or breastfeeding, ask a healthcare professional before use.

Keep out of the reach of children.

PREGNANCY OR BREAST FEEDING

If pregnant or breastfeeding, ask a healthcare professional before use.

DIRECTIONS

Place drops under tongue 30 minutes before/after meals. Adults and children 12 years and over: Take 10 drops up to 3 times per day. Consult a physician for use in children under 12 years of age.

OTHER INFORMATION

Tamper resistant. If seal is broken, do not use. After opening, close container tightly and store at room temperature away from heat.

INACTIVE INGREDIENTS

20% ethanol, purified water.

LABEL

Est 1985

Professional Formulas

Complementary Health

Intestine Drops

Homeopathic Remedy

2 FL. OZ. (59 mL)